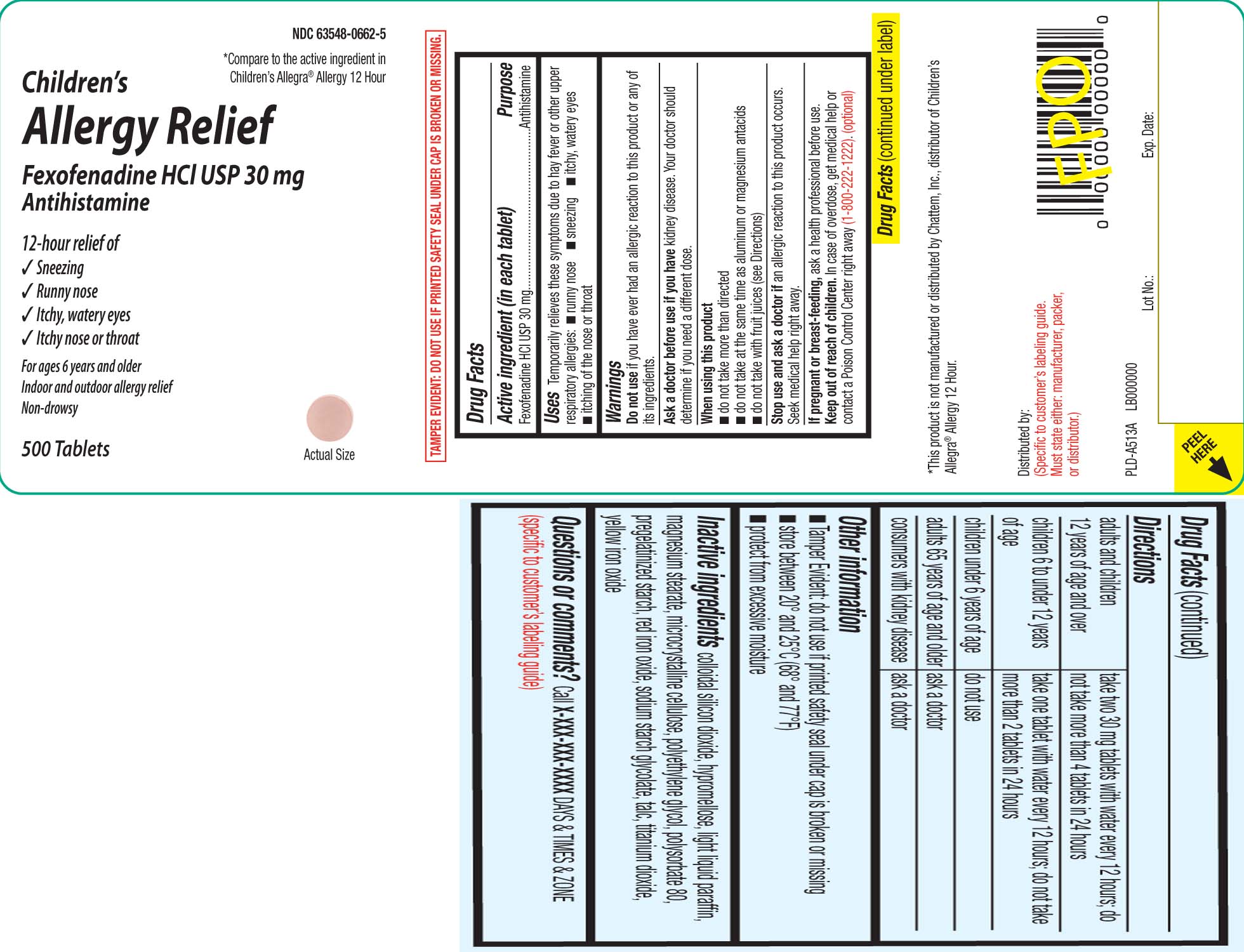 DRUG LABEL: Childrens Allergy Relief
NDC: 63548-0662 | Form: TABLET
Manufacturer: PLD Acquisitions LLC DBA Avéma Pharma Solutions
Category: otc | Type: HUMAN OTC DRUG LABEL
Date: 20230213

ACTIVE INGREDIENTS: FEXOFENADINE HYDROCHLORIDE 30 mg/1 1
INACTIVE INGREDIENTS: SILICON DIOXIDE; LIGHT MINERAL OIL; HYPROMELLOSES; FERRIC OXIDE RED; FERRIC OXIDE YELLOW; MAGNESIUM STEARATE; CELLULOSE, MICROCRYSTALLINE; POLYETHYLENE GLYCOL, UNSPECIFIED; POLYSORBATE 80; TALC; TITANIUM DIOXIDE; STARCH, CORN; SODIUM STARCH GLYCOLATE TYPE A CORN

DRUG FACTS

Active ingredient (in each tablet)

Fexofenadine HCL USP 30 mg

Purpose

Antihistamine

Uses

temporarily relieves these symptoms due to hay fever or other upper respiratory allergies:

- runny nose
- sneezing
- itchy, watery eyes
- itching of the nose or throat

Warnings

Do not use

if you have ever had an allergic reaction to this product or any of its ingredients.

Ask a doctor before use if you have

kidney disease. Your doctor should determine if you need a different dose.

When using this product

- do not take more than directed
- do not take at the same time as aluminum or magnesium antacids
- do not take with fruit juices (see Directions)

Stop use and ask a doctor if

an allergic reaction to this product occurs. Seek medical help right away.

If pregnant or breast-feeding,

ask a health professional before use.

Keep out of reach of children.

In case of overdose, get medical help or contact a Poison Control Center right away (1-800-222-1222).

Directions

adults and children 12 years of age and over | take two 30 mg tablets with water every 12 hours; do not take more than 4 tablets in 24 hours
children 6 to under 12 years of age | take one tablet with water every 12 hours; do not take more than 2 tablets in 24 hours
children under 6 years of age | do not use
adults 65 years of age and older | ask a doctor
consumers with kidney disease | ask a doctor

Other information

- Tamper Evident: do not use if printed safety seal under cap is broken or missing
- store between 20º and 25ºC (68º and 77ºF)
- protect from excessive moisture

Inactive ingredients

colloidal silicon dioxide, hypromellose, light liquid paraffin magnesium stearate, microcrystalline cellulose, polyethylene glycol, polysorbate 80, pregelatinized starch, red iron oxide, sodium starch glycolate, talc, titanium dioxide, yellow iron oxide

Principal Display Panel

*Compare to the active ingredient in Children's Allegra® Allergy 12 Hour

Children's Allergy Relief

Fexofenadine HCL USP 30 mg

Antihistamine

24 Hour Relief of:

- sneezing
- runny nose
- itchy, watery eyes
- itchy nose or throat

Indoor and outdoor allergy relief

Non-drowsy

Tablets

*This product is not manufactured or distributed by Chattem Inc., distributor of Allegra® Allergy 12 hour.

TAMPER EVIDENT: DO NOT USE IF PRINTED SAFETY SEAL UNDER CAP IS BROKEN OR MISSING.

Product Label

CHILDRENS ALLERGY RELIEF